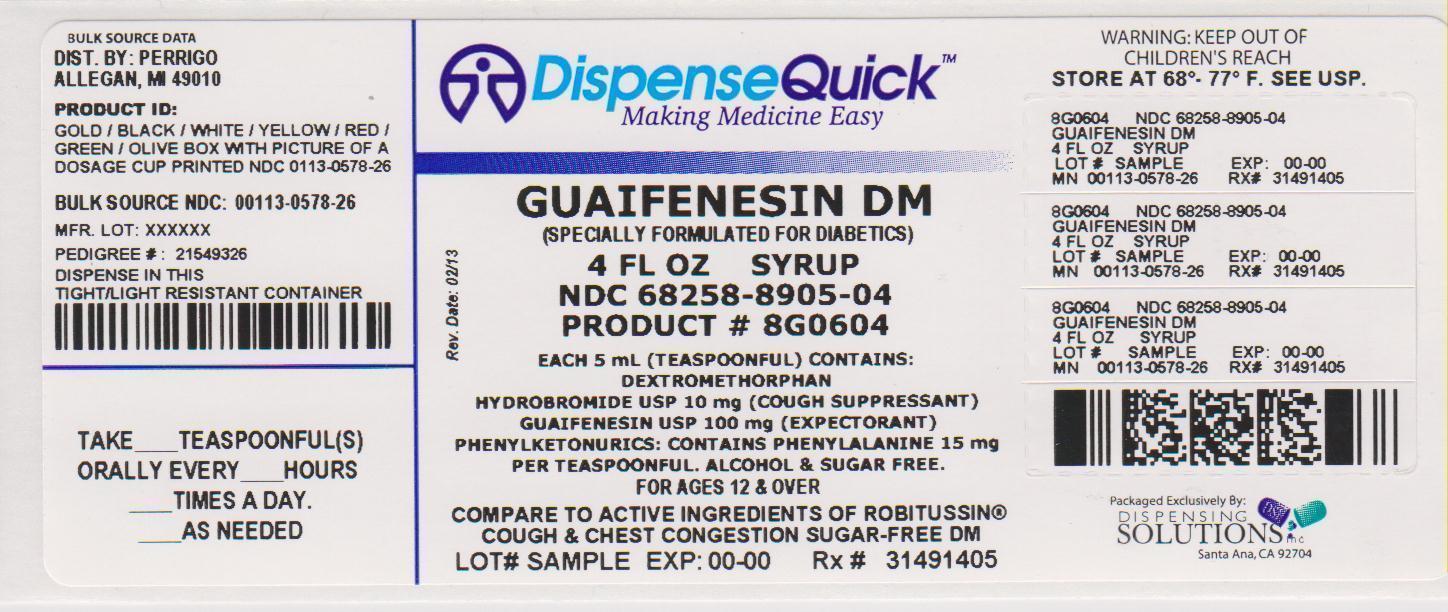 DRUG LABEL: good sense tussin dm
NDC: 68258-8905 | Form: LIQUID
Manufacturer: Dispensing Solutions, Inc.
Category: otc | Type: HUMAN OTC DRUG LABEL
Date: 20130717

ACTIVE INGREDIENTS: DEXTROMETHORPHAN HYDROBROMIDE 10 mg/5 mL; GUAIFENESIN 100 mg/5 mL
INACTIVE INGREDIENTS: ASPARTAME; BENZOIC ACID; GLYCERIN; HYDROXYETHYL CELLULOSE (5500 MPA.S AT 2%); POLYETHYLENE GLYCOLS; WATER

Perrigo Tussin DM Drug Facts

Active ingredient (in each 5 mL tsp)

Dextromethorphan HBr, USP 10 mg

Guaifenesin, USP 100 mg

Purpose

Cough suppressant

Expectorant

Uses

- temporarily relieves cough due to minor throat and bronchial irritation as may occur with a cold
- helps loosen phlegm (mucus) and thin bronchial secretions to drain bronchial tubes

Warnings

Do not use

- if you are now taking a prescription monoamine oxidase inhibitor (MAOI) (certain drugs for depression, psychiatric, or emotional conditions, or Parkinson’s disease), or for 2 weeks after stopping the MAOI drug. If you do not know if your prescription drug contains an MAOI, ask a doctor or pharmacist before taking this product.

Ask a doctor before use if you have

- cough that occurs with too much phlegm (mucus)
- cough that lasts or is chronic such as occurs with smoking, asthma, chronic bronchitis, or emphysema

Stop use and ask a doctor if

cough lasts for more than 7 days, comes back, or is accompanied by fever, rash, or persistent headache. A persistent cough may be a sign of a serious condition.

If pregnant or breast-feeding,

ask a health professional before use.

Keep out of reach of children.

In case of overdose, get medical help or contact a Poison Control Center right away.

Directions

- do not take more than 6 doses in any 24-hour period
- this adult product is not intended for use in children under 12 years of age

age | dose
adults and children; 12 years and over | 2 teaspoons; every 4 hours
children under 12 years | do not use

Other information

- Phenylketonurics: contains phenylalanine 15 mg per teaspoon
- store at 20°-25°C (68°-77°F)

Inactive ingredients

aspartame, benzoic acid, flavors, glycerin, hydroxyethyl cellulose, polyethylene glycol, purified water

Questions or comments?

1-800-719-9260

Principal Display Panel

Non-Drowsy

See New Dosing Directions

Tussin DM

Cough & Chest Congestion

Sugar-Free

Cough Suppressant (Dextromethorphan HBr)

Expectorant (Guaifenesin)

Relieves:
Coughs

Chest Congestion

Mucus

Specially Formulated for Diabetics

Adult

For Ages 12 & Over

Alcohol & Sugar Free

Compare to active ingredients of Robitussin® Cough & Chest Congestion Sugar-Free DM

NDC 68258-8905-04